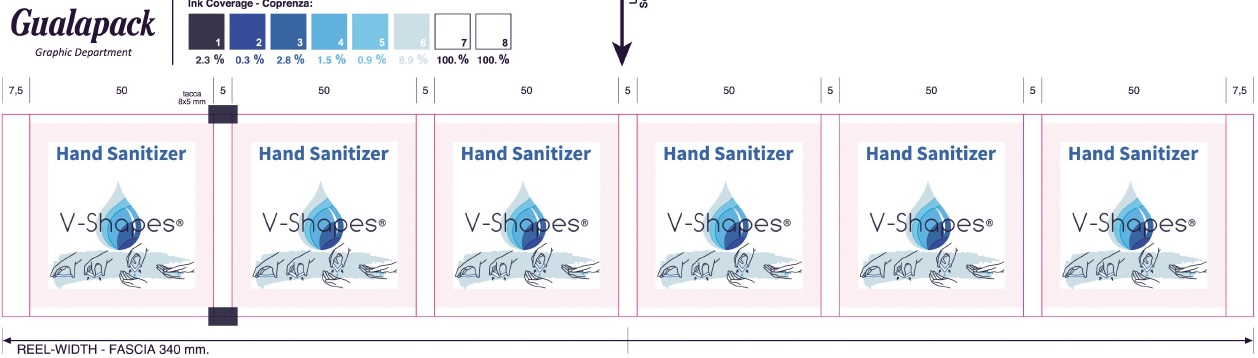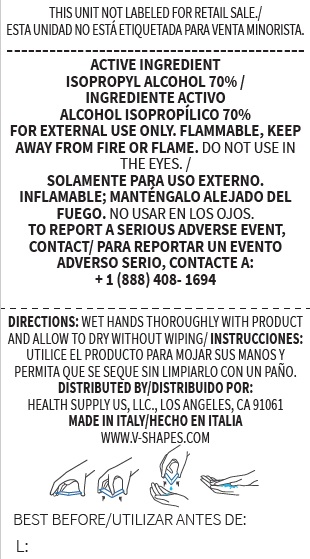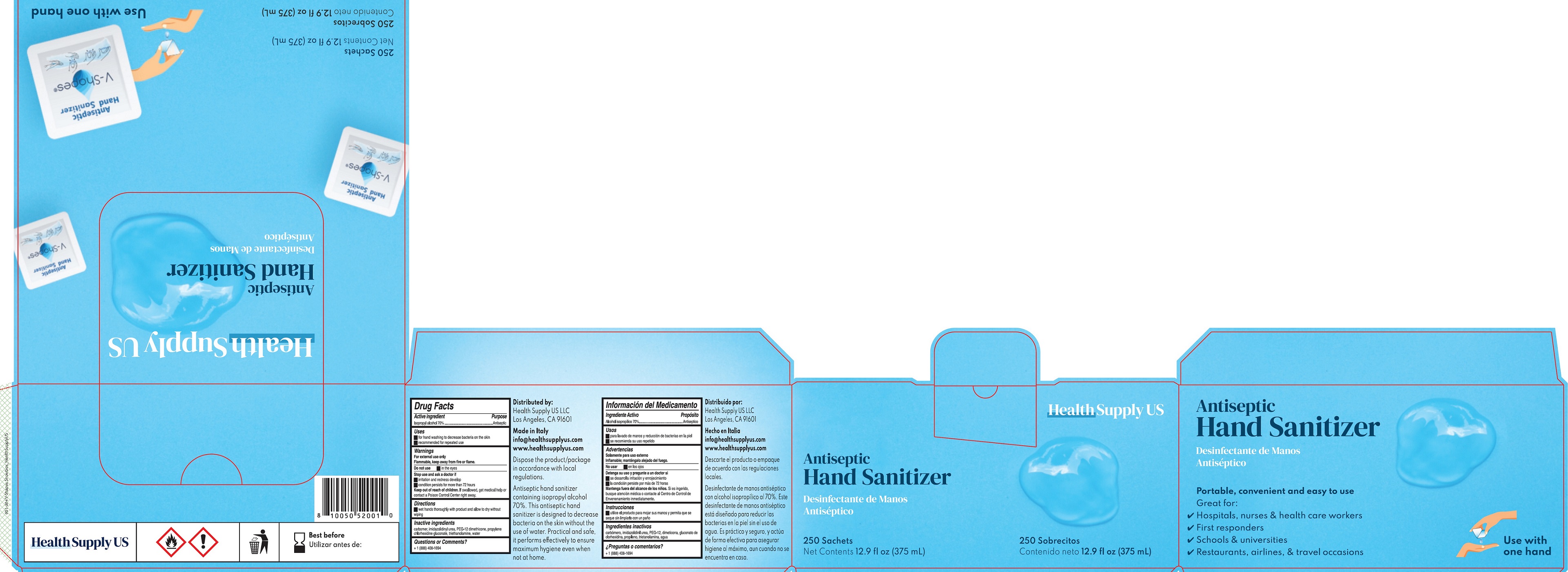 DRUG LABEL: Antiseptic Hand Sanitizer
NDC: 74785-000 | Form: GEL
Manufacturer: V-Shapes Srl
Category: otc | Type: HUMAN OTC DRUG LABEL
Date: 20200504

ACTIVE INGREDIENTS: ISOPROPYL ALCOHOL 0.7 mL/1 mL
INACTIVE INGREDIENTS: CARBOMER HOMOPOLYMER, UNSPECIFIED TYPE; IMIDUREA; PEG-12 DIMETHICONE (300 CST); TROLAMINE; WATER

Antiseptic Hand Sanitizer

Active ingredient

Isopropyl alcohol 70%

Purpose

Antiseptic

Uses

- for hand washing to decrease bacteria on the skin
- recommended for repeated use

Warnings

For external use only
Flammable, keep away from fire or flame.

Do not use

in the eyes

Stop use and ask a doctor if

- irritation and redness develop
- condition persists for more than 72 hours

Keep out of reach of children.

If swallowed, get medical help or contact a Poison Control Center right away.

Directions

wet hands thoroughly with product and allow to dry without wiping

Inactive ingredients

carbomer, imidazolidinyl urea, PEG-12 dimethicone, propylene chlorhexidine gluconate, triethanolamine, water

Questions or Comments?

+1 (888) 408-1694